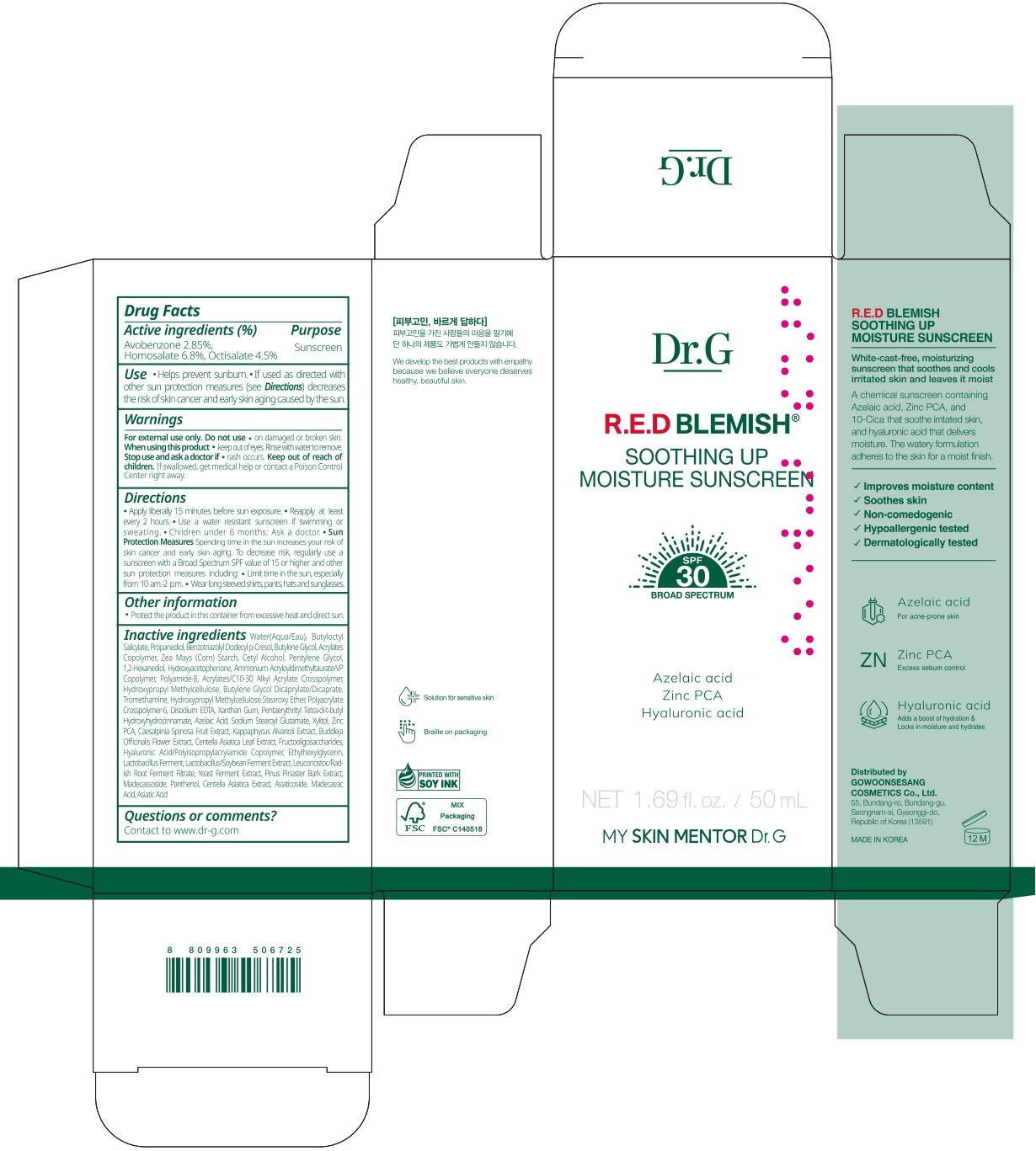 DRUG LABEL: Dr.G R.E.D BLEMISH SOOTHING UP MOISTURE SUNSCREEN
NDC: 51621-023 | Form: CREAM
Manufacturer: GOWOONSESANG COSMETICS CO., LTD.
Category: otc | Type: HUMAN OTC DRUG LABEL
Date: 20250321

ACTIVE INGREDIENTS: HOMOSALATE 6.8 g/100 mL; OCTISALATE 4.5 g/100 mL; AVOBENZONE 2.85 g/100 mL
INACTIVE INGREDIENTS: XANTHAN GUM; SODIUM STEAROYL GLUTAMATE; LEUCONOSTOC/RADISH ROOT FERMENT FILTRATE; MARITIME PINE; CENTELLA ASIATICA TRITERPENOIDS; BUTYLOCTYL SALICYLATE; AMMONIUM ACRYLOYLDIMETHYLTAURATE/VP COPOLYMER; 1,2-HEXANEDIOL; BUTYLENE GLYCOL DICAPRYLATE/DICAPRATE; EDETATE DISODIUM; TARA SPINOSA FRUIT; ASIATICOSIDE; ASIATIC ACID; BUDDLEJA OFFICINALIS FLOWER; MADECASSIC ACID; PROPANEDIOL; HYDROXYACETOPHENONE; CENTELLA ASIATICA LEAF; MADECASSOSIDE; WATER; POLYAMIDE-8 (4500 MW); AZELAIC ACID; ETHYLHEXYLGLYCERIN; BUTYLENE GLYCOL; CETYL ALCOHOL; HYDROXYPROPYL METHYLCELLULOSE; PENTAERYTHRITYL TETRA-DI-T-BUTYL HYDROXYHYDROCINNAMATE; KAPPAPHYCUS ALVAREZII; BENZOTRIAZOLYL DODECYL P-CRESOL; ZEA MAYS (CORN) STARCH; POLYACRYLATE CROSSPOLYMER-6; PENTYLENE GLYCOL; TROMETHAMINE; PANTHENOL; BUTYL ACRYLATE/METHYL METHACRYLATE/METHACRYLIC ACID COPOLYMER (18000 MW); XYLITOL; ZINC PCA

Active ingredients

Avobenzone 2.85%,
Homosalate 6.8%, Octisalate 4.5%

Purpose

Sunscreen

Use

- Helps prevent sunburn.
- If used as directed with other sun protection measures (see Directions) decreases the risk of skin cancer and earty skin aging caused by the sun.

Warnings

For externall use only. Do not use

- on damaged or broken skin.

When using this product

- keep out of eyes. Rinse with water to remove.

Stop use and ask a doctor if

- rash occurs.

Keep out of reach of children.

If swallowed, get medical help or contact a Poison Control Center right away.

Directions

- Apply liberally 15 minutes before sun exposure.
- Reapply at least every 2 hours.
- Use a water resistant sunscreen if swimming or sweating.
- Children under 6 months: Ask a doctor.
- Sun Protection Measures Spending time in the sun increases your risk of skin cancer and early skin aging. To decrease risk, regularly use a sunscreen with a Broad Spectrum SPF value of 15 or higher and other sun protection measures including:
- Limit time in the sun, especiall from 10 am-2 p.m.
- Wear long sleeved shirts, pants, hats and sunglasses.

Other information

- Protect the product in this container from excessive heat and direct sun.

Inactive ingredients

Water(Aqua/Eau), Butyloctyl Salicylate, Propanediol, Benzotriazolyl Dodecyl p-Cresol, Butylene Glycol, Acrylates Copolymer, Zea Mays (Corn) Starch, Cetyl Alcohol, Pentylene Glycol, 1,2-Hexanediol, Hydroxyacetophenone, Ammonium Acryloyldimethyltaurate/VP
Copolymer, Polyamide-8, Acrylates/C10-30 Alkyl Acrylate Crosspolymer, Hydroxypropyl Methylcellulose, Butylene Glycol Dicaprylate/Dicaprate, Tromethamine, Hydroxypropyl Methylcellulose Stearoxy Ether, Polyacrylate Crosspolymer-6, Disodium EDTA, Xanthan Gum, Pentaerythrityl Tetra-di-t-butyl Hydroxyhydrocinnamate, Azelaic Acid, Sodium Stearoyl Glutamate, Xylitol, Zinc PCA, Caesalpinia Spinosa Fruit Extract, Kappaphycus Alvarezii Extract, Buddleja Officinalis Flower Extract, Centella Asiatica Leaf Extract, Fructooligosaccharides, Hyaluronic Acid/Polyisopropylacrylamide Copolymer, Ethylhexylglycerin, Lactobacillus Ferment, Lactobacillus/Soybean Ferment Extract, Leuconostoc/Radish Root Ferment Filtrate, Yeast Ferment Extract, Pinus Pinaster Bark Extract, Madecassoside, Panthenol, Centella Asiatica Extract, Asiaticoside, Madecassic Acid, Asiatic Acid

Questions or comments?

Contact to www.dr-g.com